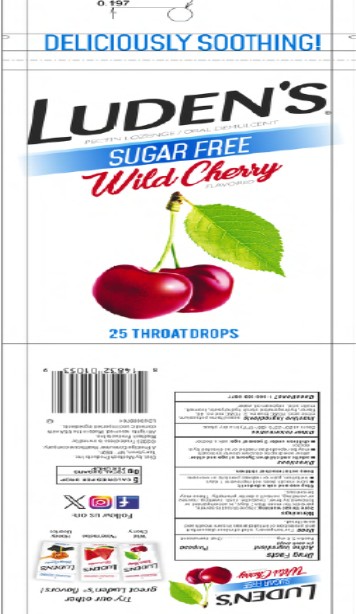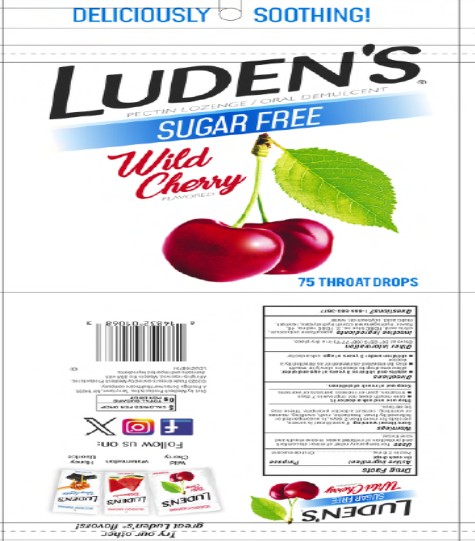 DRUG LABEL: LUDENS SUGAR FREE WILD CHERRY THROAT
NDC: 52183-249 | Form: LOZENGE
Manufacturer: Prestige Brands Holdings, Inc.
Category: otc | Type: HUMAN OTC DRUG LABEL
Date: 20250909

ACTIVE INGREDIENTS: PECTIN 2.8 mg/1 1
INACTIVE INGREDIENTS: ACESULFAME POTASSIUM; CITRIC ACID MONOHYDRATE; FD&C BLUE NO. 2; FD&C RED NO. 40; HYDROGENATED STARCH HYDROLYSATE; ISOMALT; MALIC ACID; SOYBEAN OIL; WATER

Ludens Sugar Free Wild Cherry

Drug Facts

Active ingredient

(in each drop)

Pectin 2.8 mg

Purpose

Oral Demulcent

Uses

For temporary relief of minor discomfort and protection of irritated areas in sore mouth and sore throat

Warnings

Sore throat warning: if sore throat is severe, persists for more than 2 days, is accompanied or followed by fever, headache, rash, swelling, nausea or vomiting, consult a doctor promptly. These may be serious.

Stop use and ask a doctor if

- sore mouth does not improve in 7 days
- irritation, pain or redness persists or worsens

Directions

- adults and children 3 years of age and older: allow one drop to dissolve slowly in mouth.
- may be repeated as needed or as directed by a doctor.
- children under 3 years of age: ask a doctor.

Other information

- store at 20-25ºC (68-77ºF) in a dry place

Inactive ingredients

acesulfame potassium, citric acid, FD&C blue no.2, FD&C red no. 40, hydrogenated starch hydrolysate, isomalt, malic acid, soybean oil,water

Questions or comments?

call 1-866-583-3677 Ludens.com

PRINCIPAL DISPLAY PANEL

Sugar Free
LUDEN’S® WILD CHERRY
25 Drops

PRINCIPAL DISPLAY PANEL

Sugar Free
LUDEN’S® WILD CHERRY
75 Drops